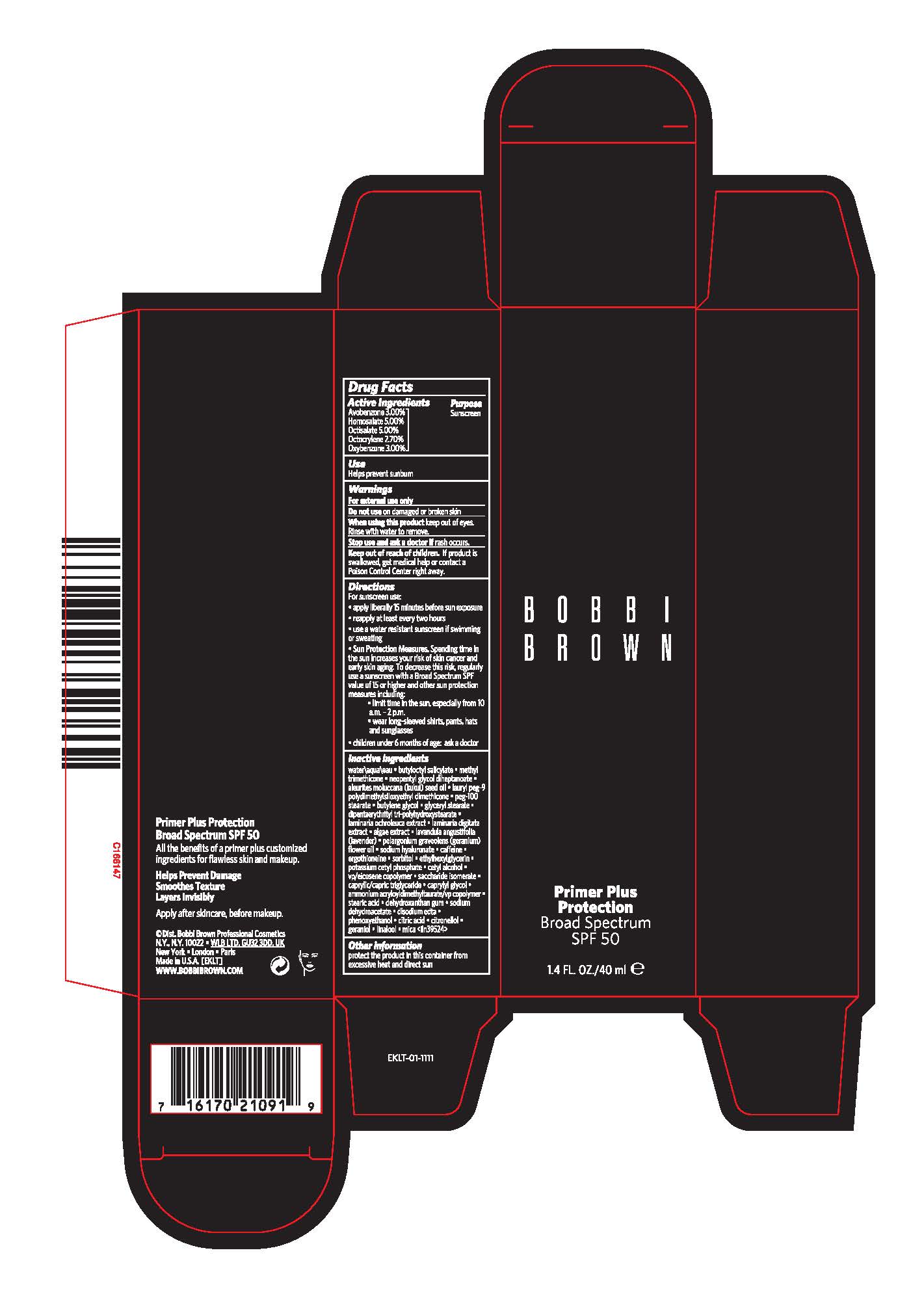 DRUG LABEL: BOBBI BROWN PRIMER PLUS PROTECTION BROAD SPECTRUM SPF50
NDC: 64141-035 | Form: CREAM
Manufacturer: Bobbi Brown Professional Cosmetics Inc.
Category: otc | Type: HUMAN OTC DRUG LABEL
Date: 20241213

ACTIVE INGREDIENTS: OCTISALATE 50 mg/1 mL; OCTOCRYLENE 27 mg/1 mL; HOMOSALATE 50 mg/1 mL; OXYBENZONE 30 mg/1 mL; AVOBENZONE 30 mg/1 mL
INACTIVE INGREDIENTS: DEHYDROXANTHAN GUM; CITRIC ACID MONOHYDRATE; MICA; WATER; SODIUM DEHYDROACETATE; GERANIOL; GLYCERYL MONOSTEARATE; LAVANDULA ANGUSTIFOLIA FLOWERING TOP; POTASSIUM CETYL PHOSPHATE; CAPRYLYL GLYCOL; SACCHARIDE ISOMERATE; METHYL TRIMETHICONE; BUTYLENE GLYCOL; NEOPENTYL GLYCOL DIHEPTANOATE; LAMINARIA OCHROLEUCA; LAMINARIA DIGITATA; CETYL ALCOHOL; KUKUI NUT OIL; LAURYL PEG-9 POLYDIMETHYLSILOXYETHYL DIMETHICONE; PEG-100 STEARATE; DIPENTAERYTHRITYL TRI-POLYHYDROXYSTEARATE; CAFFEINE; SORBITOL; VINYLPYRROLIDONE/EICOSENE COPOLYMER; STEARIC ACID; EDETATE DISODIUM; PHENOXYETHANOL; .BETA.-CITRONELLOL, (R)-; LINALOOL, (+/-)-; PORPHYRIDIUM PURPUREUM; HYALURONATE SODIUM; ETHYLHEXYLGLYCERIN; BUTYLOCTYL SALICYLATE; PELARGONIUM GRAVEOLENS FLOWER OIL; ERGOTHIONEINE; MEDIUM-CHAIN TRIGLYCERIDES; AMMONIUM ACRYLOYLDIMETHYLTAURATE/VP COPOLYMER

BOBBI BROWN PRIMER PLUS PROTECTION BROAD SPECTRUM SPF50

Active Ingredients

Avobenzone 3.00%

Homosalate 5.00%

Octisalate 5.00%

Octocrylene 2.70%

Oxybenzone 3.00%

Purpose

Sunscreen

Use

Helps prevent sunburn

Warnings

For External use only

Do Not Use

on damaged or broken skin

When using this product

keep out of eyes. Rinse with water to remove.

Stop use and ask a doctor if

rash occurs

Keep out of reach of children.

If product is swallowed, get medical help or contact a Poison Control Center right away.

Directions

For sunscreen use:

apply liberally 15 minutes before sun exposure
reapply at least every two hours
use a water resistant sunscreen if swimming or sweating
Sun Protection Measures. Spending time in the sun increases your risk of skin cancer and early skin aging. To decrease this risk, regularly use a sunscreen with a Broad Spectrum SPF value of 15 or higher and other sun protection measures including:

limit time in the sun, especially from 10 a.m.-2 p.m.
wear long-sleeved shirts, pants, hats and sunglasses

children under 6 months of age:
ask a doctor

Inactive Ingredients

WATER\AQUA\EAU,BUTYLOCTYL SALICYLATE,METHYL TRIMETHICONE,NEOPENTYL GLYCOL DIHEPTANOATE,ALEURITES MOLUCCANA (KUKUI) SEED OIL,LAURYL PEG-9 POLYDIMETHYLSILOXYETHYL DIMETHICONE,PEG-100 STEARATE,BUTYLENE GLYCOL,GLYCERYL STEARATE,DIPENTAERYTHRITYL TRI-POLYHYDROXYSTEARATE,LAMINARIA OCHROLEUCA EXTRACT,LAMINARIA DIGITATA EXTRACT,ALGAE EXTRACT,LAVANDULA ANGUSTIFOLIA (LAVENDER),PELARGONIUM GRAVEOLENS (GERANIUM) FLOWER OIL,SODIUM HYALURONATE,CAFFEINE,ERGOTHIONEINE,SORBITOL,ETHYLHEXYLGLYCERIN,POTASSIUM CETYL PHOSPHATE,CETYL ALCOHOL,VP/EICOSENE COPOLYMER,SACCHARIDE ISOMERATE,CAPRYLIC/CAPRIC TRIGLYCERIDE,CAPRYLYL GLYCOL,AMMONIUM ACRYLOYLDIMETHYLTAURATE/VP COPOLYMER,STEARIC ACID,DEHYDROXANTHAN GUM,SODIUM DEHYDROACETATE,DISODIUM EDTA,PHENOXYETHANOL,CITRIC ACID,CITRONELLOL,GERANIOL,LINALOOL,MICA <ILN39524>

Other Information

protect the product in this container from excessive heat and direct sun

PACKAGE LABEL

BOBBI
BROWN

Primer Plus Protection
BROAD
SPECTRUM
SPF 50

1.4 FL. OZ/40 ML e